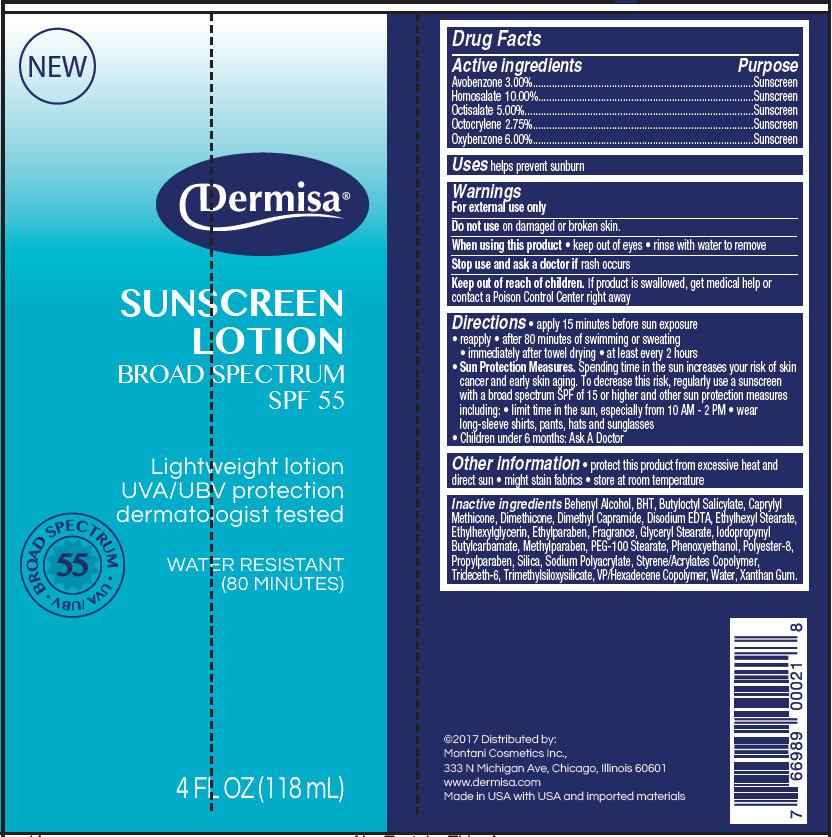 DRUG LABEL: Dermisa SUNSCREEN SPF 55
NDC: 68343-003 | Form: LOTION
Manufacturer: Montani Cosmetics Inc
Category: otc | Type: HUMAN OTC DRUG LABEL
Date: 20170911

ACTIVE INGREDIENTS: OCTOCRYLENE 2.75 g/100 mL; AVOBENZONE 3 g/100 mL; OXYBENZONE 6 g/100 mL; OCTISALATE 5 g/100 mL; HOMOSALATE 10 g/100 mL
INACTIVE INGREDIENTS: VINYLPYRROLIDONE/HEXADECENE COPOLYMER; WATER; TRIDECETH-6; SODIUM POLYACRYLATE (8000 MW); SILICON DIOXIDE; DOCOSANOL; BUTYLATED HYDROXYTOLUENE; BUTYLOCTYL SALICYLATE; CAPRYLYL TRISILOXANE; DIMETHICONE; DIMETHYL CAPRAMIDE; EDETATE DISODIUM ANHYDROUS; ETHYLHEXYL STEARATE; ETHYLHEXYLGLYCERIN; ETHYLPARABEN; GLYCERYL STEARATE SE; IODOPROPYNYL BUTYLCARBAMATE; METHYLPARABEN; PEG-100 STEARATE; PHENOXYETHANOL; POLYESTER-8 (1400 MW, CYANODIPHENYLPROPENOYL CAPPED); PROPYLPARABEN; TRIMETHYLSILOXYSILICATE (M/Q 0.6-0.8); XANTHAN GUM

Drug Facts

Active Ingredients

Avobenzone 3.00%

Homosalate 10.00%

Octisalate 5.00%

Octocrylene 2.75%

Oxybenzone 6.00%

Purpose

Sunscreen

Sunscreen

Sunscreen

Sunscreen

Sunscreen

Uses

helps prevent sunburn

Warnings

For external use only

Do not use on damaged or broken skin

When using this product

• keep out of eyes • rinse with water to remove

Stop use and ask a doctor if

rash occurs

Keep out of reach of children

If product is swallowed, get medical help or contact a Poison Control Center right away.

Directions

• apply 15 minutes before sun exposure • reapply • after 80 minutes of swimming or sweating • immediately after towel drying • at least every 2 hours • Sun Protection Measures. Spending time in the sun increases your risk of skin cancer and early skin aging. To decrease this risk, regularly use a sunscreen with a broad spectrum SPF of 15 or higher and other sun protection measures including: • limit time in sun, especially from 10 a.m.- 2 p.m. • wear long-sleeve shirts, pants, hats, and sunglasses

• Children under 6 months: Ask a Doctor

Other information

• protect this product from excessive heat and direct sun • might stain fabrics • store at room temperature

Inactive Ingredients

Behenyl Alcohol, BHT, Butyloctyl Salicylate, Caprylyl Methicone, Dimethicone, Dimethyl Capramide, Disodium EDTA, Ethylhexyl Stearate, Ethylhexylglycerin, Ethylparaben, Fragrance, Glyceryl Stearate, Iodopropynyl Butylcarbamate, Methylparaben, PEG-100 Stearate, Phenoxyethanol, Polyester-8, Propylparaben, Silica, Sodium Polyacrylate, Styrene/Acrylates Copolymer, Trideceth-6, Trimethylsiloxysilicate, VP/Hexadecene Copolymer, Water, Xanthan Gum